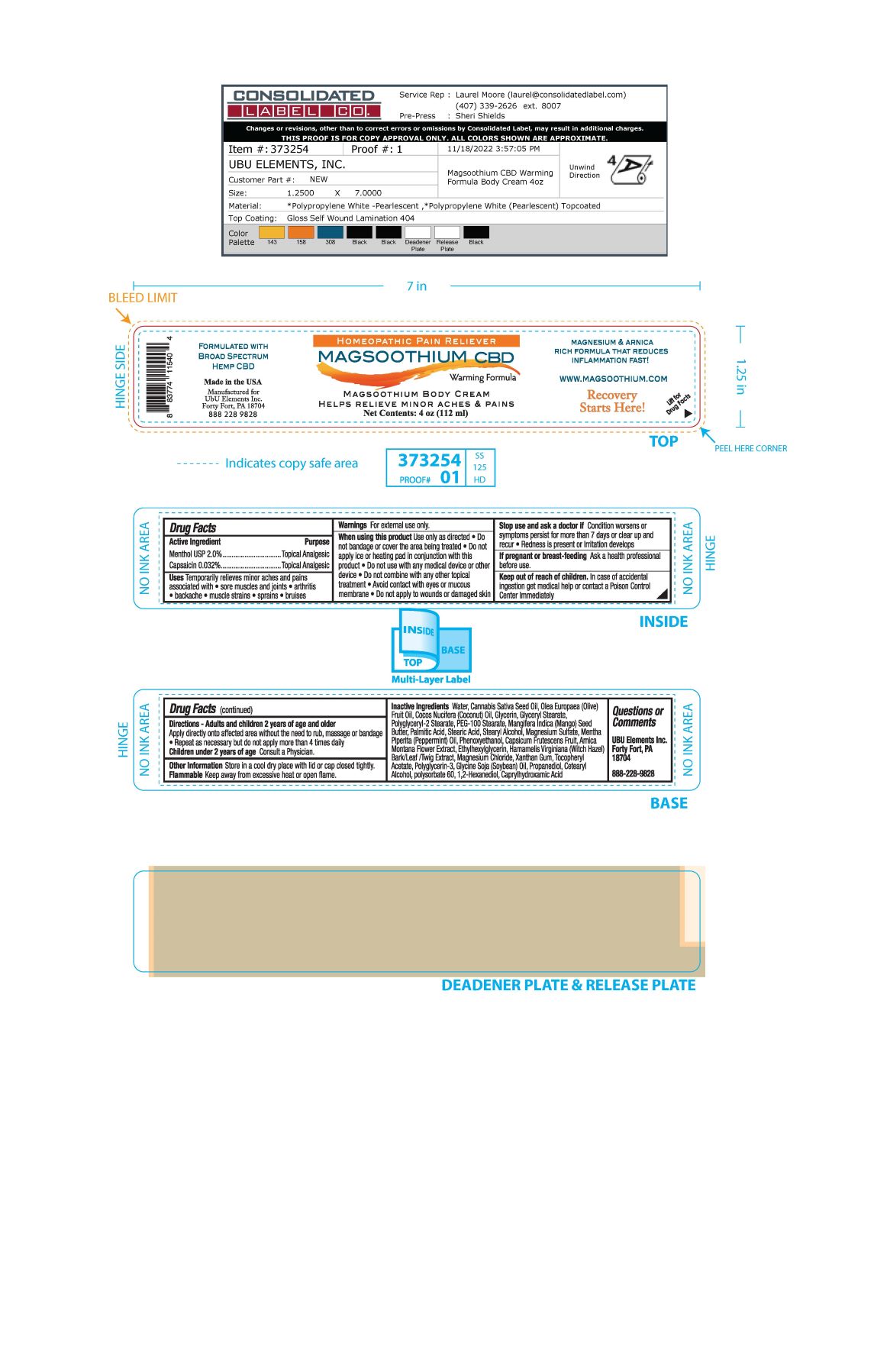 DRUG LABEL: Magsoothium Body
NDC: 83262-001 | Form: CREAM
Manufacturer: Ubu/Elements, Inc.
Category: otc | Type: HUMAN OTC DRUG LABEL
Date: 20251215

ACTIVE INGREDIENTS: CAPSAICIN 0.032 g/100 mL; MENTHOL 2 g/100 mL
INACTIVE INGREDIENTS: POLYGLYCERYL-2 STEARATE; MAGNESIUM SULFATE, UNSPECIFIED; MAGNESIUM CHLORIDE; ARNICA MONTANA FLOWER; PROPANEDIOL; POLYSORBATE 60; PALMITIC ACID; 1,2-HEXANEDIOL; CAPRYLHYDROXAMIC ACID; SOYBEAN OIL; CETOSTEARYL ALCOHOL; .ALPHA.-TOCOPHEROL ACETATE; WATER; CANNABIS SATIVA SEED OIL; OLIVE OIL; COCONUT OIL; POLYGLYCERIN-3; PEPPERMINT OIL; PHENOXYETHANOL; ETHYLHEXYLGLYCERIN; MANGIFERA INDICA SEED BUTTER; STEARIC ACID; PEG-100 STEARATE; TABASCO PEPPER; XANTHAN GUM; GLYCERIN; GLYCERYL MONOSTEARATE; STEARYL ALCOHOL; HAMAMELIS VIRGINIANA LEAF

Magsoothium Body Cream

Active Ingredient

Menthol USP 2.0%

Capsaicin 0.032%

Purpose
Topical Analgesic

PURPOSE

Uses Temporary relieves minor aches and pains associated with

- Sore muscles and joints
- arthritis
- backache
- muscle strains
- sprains
- bruises

Keep out of reach of children. In case of accidental ingestion get medical help or contact a Poison Control Center immediately

Stop use and ask a doctor if Condition worsens or symptoms persist for more than 7 days or clear up and recur

Redness is present or irritation develops

Warnings For external use only

When using this product use only as directed

- Do not bandage or cover the area being treated
- Do not apply ice or heating pad in conjunction with this product.
- Do not use with any medical device or other device
- Do not combine with any other topical treatment
- Avoid contact with eyes or mucous membrane
- Do not apply to wounds or damaged skin

If pregnant or breast-feeding Ask a health professional before use

DOSAGE AND ADMINISTRATION

Directions - Adults and children 2 years of age and older

Apply directly onto affected area without the need to rub, massage or bandage

- repeat as necessary but do not apply more than 4 times daily

Children under 2 years of age Consult a physician

INACTIVE INGREDIENT

Inactive Ingredients Water, Cannabis Sativa Seed Oil, Olea Europaea (Olive) Fruit Oil, Cocos Nucifera (Coconut) Oil, Glycerin, Glyceryl Stearate, Polyglyceryl-2 Stearate, PEG-100 Stearate, Mangifera indica (Mango) Seed Butter, Palmitic Acid, Stearic Acid, Stearyl Alcohol, Magnesium Sulfate, Mentha Piperita (Peppermint) Oil, Phenoxyethanol, Capsicum Frutescens Fruit, Arnica Montana Flower Extract, Ethylhexylglycerin, Hamamelis Virginiana (Witch Hazel) Bark/Leaf/Twig Extract, Magnesium Chloride, Xanthan Gum, Tocopheryl Acetate, Polyglycerin-3, Glycine Soja (Soybean) Oil, Propanediol, Cetearyl Acohol, Polysorbate 60, 1,2-Hexanediol, Caprylhydroxamic Acid

PACKAGE LABEL

Homeopathic Pain Reliever

Magsoothium CBD Warming Formula

Magsoothium Body Cream

Helps relieve minor aches & pains

Net Contents: 4 oz (112 ml)